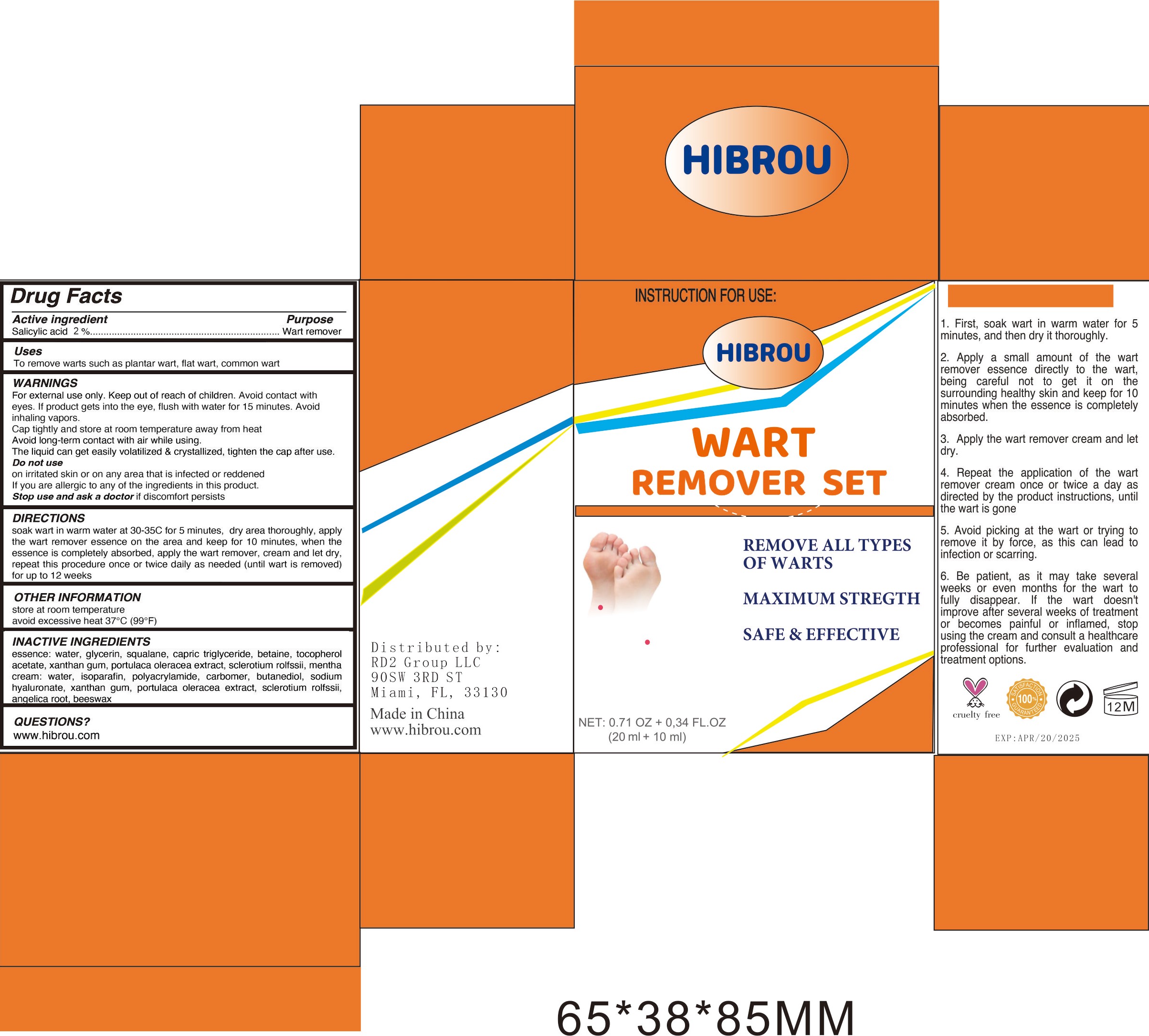 DRUG LABEL: Wart Remover set
NDC: 83436-001 | Form: OIL
Manufacturer: RD2 GROUP, LLC
Category: otc | Type: HUMAN OTC DRUG LABEL
Date: 20230504

ACTIVE INGREDIENTS: SALICYLIC ACID 2 mg/100 mL
INACTIVE INGREDIENTS: WATER; SQUALANE; GREEN TEA LEAF; BETAINE; CETOSTEARYL ALCOHOL; ISONONYL ISONONANOATE; CHONDRUS CRISPUS; HYDROXYETHYL UREA; DIMETHICONE; TREHALOSE; ERYTHRITOL; .ALPHA.-TOCOPHEROL ACETATE, D-; 1,2-HEXANEDIOL; HYDROXYACETOPHENONE; CETEARYL GLUCOSIDE; ALLANTOIN; POTASSIUM CETYL PHOSPHATE; CARBOMER COPOLYMER TYPE A; HYDROXYPINACOLONE RETINOATE; XANTHAN GUM; LAURETH-7; MEDIUM-CHAIN TRIGLYCERIDES; PROPYLENE GLYCOL; DIMETHYL ISOSORBIDE; TROLAMINE; GLYCERIN; GLYCERYL MONOSTEARATE

83436-001
Wart Remover set

Active Ingredient

Salycilic Acid 2%

Purpose

wart remover

Use

To remove warts such as plantar wart, flat wart, common wart

Warnings

For external use only. Keep out of reach of children. Avoid contact with
eyes. If product gets into the eye, flush with water for 15 minutes. Avoid
inhaling vapors.
Cap tightly and store at room temperature away from heat
Avoid long-term contact with air while using.
The liquid can get easily volatilized & crystallized, tighten the cap after use.

Do not use

on irritated skin or on any area that is infected or reddened
If you are allergic to any of the ingredients in this product.

WHEN USING

Only on the wart

STOP USE

if discomfort persists

KEEP OUT OF REACH OF CHILDREN

Directions

soak wart in warm water at 30-35C for 5 minutes, dry area thoroughly, apply
the wart remover essence on the area and keep for 10 minutes, when the
essence is completely absorbed, apply the wart remover, cream and let dry,
repeat this procedure once or twice daily as needed (until wart is removed)
for up to 12 weeks

Inactive ingredients

Water, Glycerin, Squalane, Caprylic Capric Triglyceride, Propylene Glycol, camellia sinensis leaf extract, Betaine, Cetearyl alcohol, Isononyl isononanoate, CHONDRUS CRISPUS, Hydroxyethyl urea, Polydimethylsiloxane, Trehalose, Erythritol, butyrospermum parkii extract, Isosorbide dimethyl ether, Glyceryl stearate, Tocopherol Acetate, 1,2-Hexanediol, P-hydroxyacetophenone, Cetearyl glucoside, Allantoin, Potassium cetyl phosphate, Carbomer, Hydroxypinacolone retinoate, Triethanolamine, portulaca oleracea l. Extract, Xanthan gum, Laureth-7

PACKAGE LABEL

83436-001-01